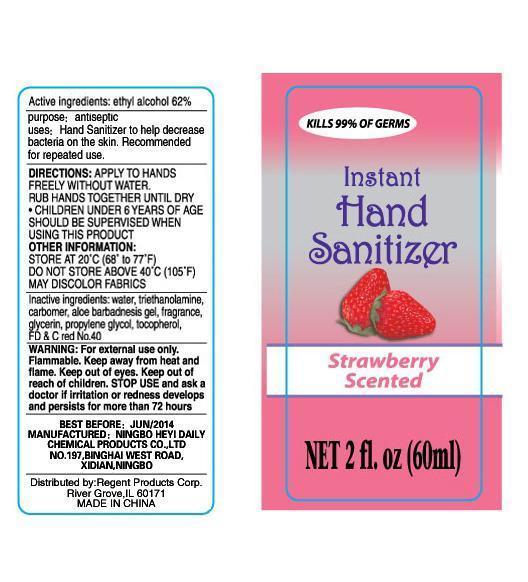 DRUG LABEL: Instant Hand Sanitizer Strawberry Scented
NDC: 51335-006 | Form: LIQUID
Manufacturer: Ningbo Heyi Daily Chemical Products Co., Ltd.
Category: otc | Type: HUMAN OTC DRUG LABEL
Date: 20120803

ACTIVE INGREDIENTS: ALCOHOL 62 mL/100 mL
INACTIVE INGREDIENTS: WATER 34.289 mL/100 mL; PROPYLENE GLYCOL; TROLAMINE; CARBOMER HOMOPOLYMER TYPE A; ALOE VERA LEAF; GLYCERIN; ALPHA-TOCOPHEROL; FD&C RED NO. 40

Drug Fact

Active Ingredient

Ethyl Alcohol 62%

Purpose:

Antiseptic

Uses:
* Hand Sanitizer to help decrease bacteria on the skin.
* Recommended for repeated use.

Warnings:
For external use only
Flammable
Keep away from fire or flame
Keep out of eyes

Keep out of Reach of Children
Children must be supervised in use of this product

Stop use and seek a doctor if redness or irritation develop and persist for more than 72 hours.

Directions:
Apply to hands freely without water. Rub hands together until dry. Children under 6 years of age should be supervised when using this product.

Other Information
Store at 20C (68-77F)
Do not store above 40C (105F)
May discolor fabrics

Inactive Ingredients:
Water, Triethanolamine, Carbomer, Aloe Barbadensis Gel, Glycerin, Propylene Glycol, Tocopherol, FD and C Red No. 40.

label